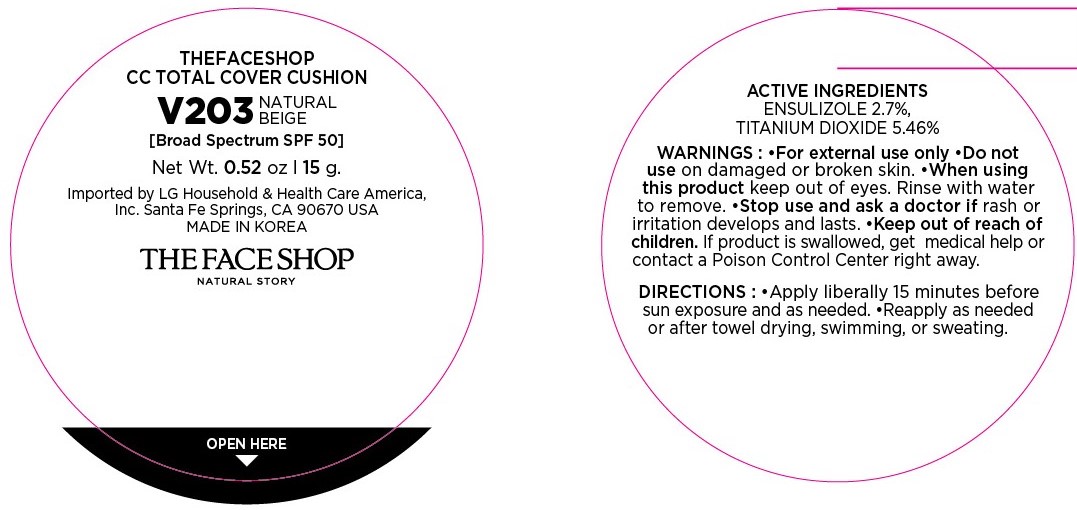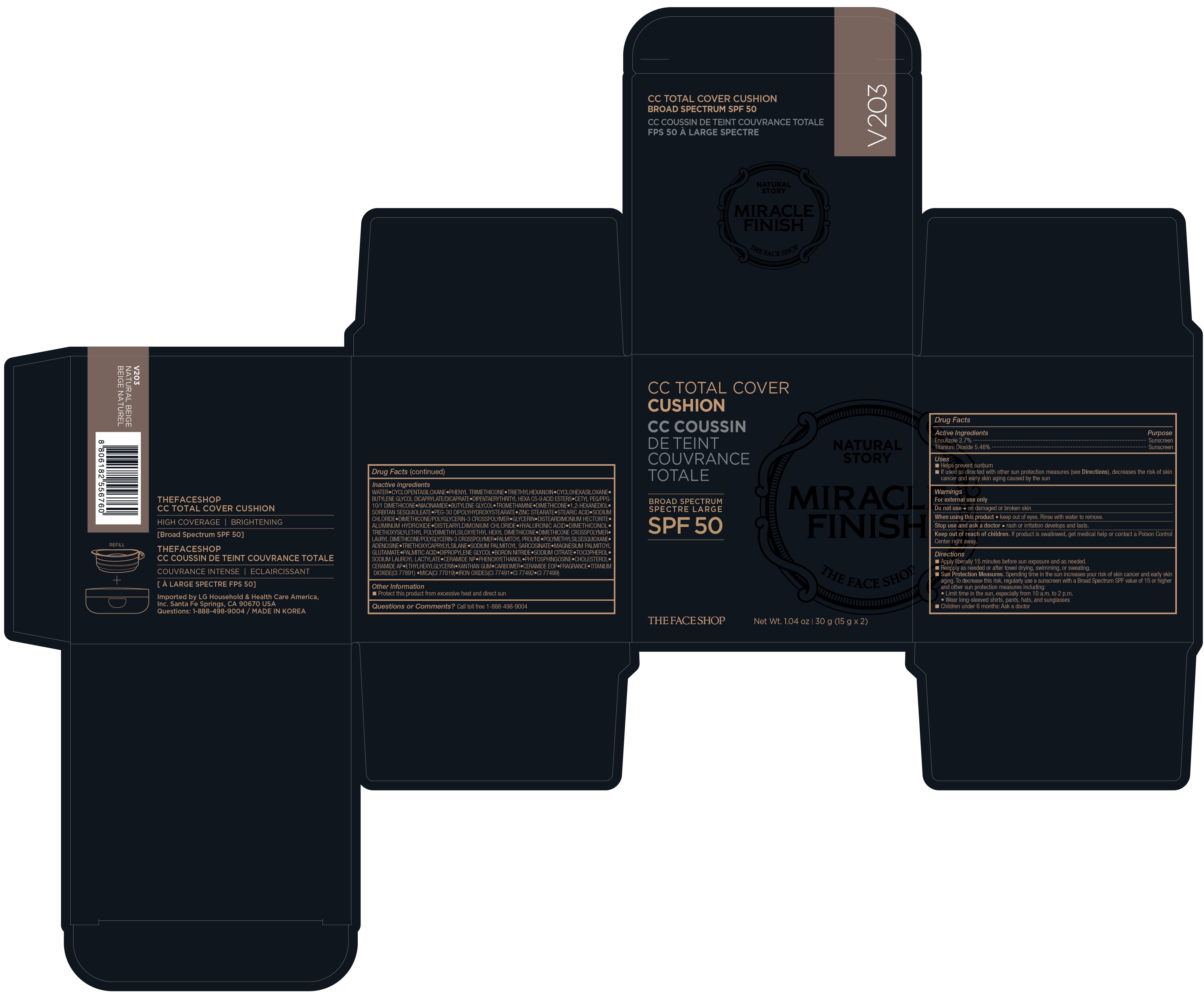 DRUG LABEL: CC Total Cover Cushion
NDC: 51523-061 | Form: POWDER
Manufacturer: THEFACESHOP Co., Ltd.
Category: otc | Type: HUMAN OTC DRUG LABEL
Date: 20210101

ACTIVE INGREDIENTS: TITANIUM DIOXIDE 0.819 g/15 g; ENSULIZOLE 0.405 g/15 g
INACTIVE INGREDIENTS: CERAMIDE 1; .ALPHA.-TOCOPHEROL ACETATE; PALMITOYL PROLINE; PHENYL TRIMETHICONE; ADENOSINE; MAGNESIUM PALMITOYL GLUTAMATE; PALMITIC ACID; CYCLOMETHICONE 6; BUTYLENE GLYCOL DICAPRYLATE/DICAPRATE; MICA; TRIETHOXYCAPRYLYLSILANE; SODIUM PALMITOYL SARCOSINATE; DIPENTAERYTHRITYL HEXA C5-9 ACID ESTERS; DIMETHICONE; BUTYLENE GLYCOL; SODIUM CHLORIDE; WATER; GLYCERIN; DIMETHICONOL (100000 CST); DIMETHICONE/VINYL DIMETHICONE CROSSPOLYMER (HARD PARTICLE); ZINC STEARATE; DISTEARDIMONIUM HECTORITE; SORBITAN SESQUIOLEATE; ALUMINUM HYDROXIDE; DISTEARYLDIMONIUM CHLORIDE; 1,2-HEXANEDIOL; TRIETHYLHEXANOIN; HYALURONIC ACID; CETYL PEG/PPG-10/1 DIMETHICONE (HLB 2); NIACINAMIDE; TROMETHAMINE; STEARIC ACID; PEG-30 DIPOLYHYDROXYSTEARATE; DIMETHICONE/VINYL DIMETHICONE CROSSPOLYMER (SOFT PARTICLE); DIPROPYLENE GLYCOL; SODIUM CITRATE; DIMETHICONE CROSSPOLYMER (450000 MPA.S AT 12% IN CYCLOPENTASILOXANE); POLYMETHYLSILSESQUIOXANE (4.5 MICRONS); TOCOPHEROL; SODIUM LAUROYL LACTYLATE; PHENOXYETHANOL; CERAMIDE AP; ETHYLHEXYLGLYCERIN; BORON NITRIDE; CERAMIDE NP; PHYTOSPHINGOSINE; CHOLESTEROL; XANTHAN GUM; CARBOMER 940

ACTIVE INGREDIENTS

Ensulizole 2.7%

Titanium Dioxide 5.46%

PURPOSE

SUNSCREEN

USES

- Helps prevent sunbrun
- If used as directed with other sun protection measures (see Directions), decreases the risk of skin cancer and early skin aging caused by the sun

WARNINGS

For external use only

Do not use on damaged or broken skin

When using this product keep out of eyes. Rinse with water to remove

Stop use and ask doctor if rash occurs

Keep out of reach of children. If product is swallowed, get medical help or contact a Poison Control Center right away.

DIRECTIONS

- Apply liberally 15 minutes before sun exposure and as needed.
- Reapply as needed or after towel drying, swimming, or sweating.
- Sun Protection Measures. Spending time in the sun increases your risk of skin cancer and early skin aging. To decrease this risk, regularly use a sunscreen with a Broad Spectrum SPF value of 15 or higher and other sun protection measures including:

- Limit time in the sun, especially from 10 a.m. to 2 p.m.

- Wear long-sleeved shirts, pants, hats, and sunglasses

- Children under 6 months: Ask a doctor

INACTIVE INGREDIENTS

WATER, CYCLOPENTASILOXANE, PHENYL TRIMETHICONE, TRIETHYLHEXANOIN, CYCLOHEXASILOXANE, BUTYLENE GLYCOL DICAPRYLATE/DICAPRATE, DIPENTAERYTHRITYL HEXA C5-9 ACID ESTERS, CETYL PEG/PPG-10/1 DIMETHICONE, NIACINAMIDE, BUTYLENE GLYCOL, TROMETHAMINE, DIMETHICONE, 1,2-HEXANEDIOL, SORBITAN SESQUIOLEATE, PEG-30 DIPOLYHYDROXYSTEARATE, ZINC STEARATE, STEARIC ACID, SODIUM CHLORIDE, DIMETHICONE/POLYGLYCERIN-3 CROSSPOLYMER, GLYCERIN, DISTEARDIMONIUM HECTORITE, ALUMINUM HYDROXIDE, DISTEARYLDIMONIUM CHLORIDE, HYALURONIC ACID, DIMETHICONOL, TRIETHOXYSILYLETHYL POLYDIMETHYLSILOXYETHYL HEXYL DIMETHICONE, DIMETHICONE CROSSPOLYMER, LAURYL DIMETHICONE/POLYGLYCERIN-3 CROSSPOLYMER, PALMITOYL PROLINE, POLYMETHYLSILSESQUIOXANE, ADENOSINE, TRIETHOXYCAPRYLYLSILANE, SODIUM PALMITOYL SARCOSINATE, MAGNESIUM PALMITOYL GLUTAMATE, PALMITIC ACID, DIPROPYLENE GLYCOL, BORON NITRIDE, SODIUM CITRATE, TOCOPHEROL, SODIUM LAUROYL LACTYLATE, CERAMIDE NP, PHENOXYETHANOL, PHYTOSPHINGOSINE, CHOLESTEROL, CERAMIDE AP, ETHYLHEXYLGLYCERIN, XANTHAN GUM, CARBOMER, CERAMIDE EOP, FRAGRANCE, TITANIUM DIOXIDE(CI 77891), MICA, IRON OXIDES(CI 77491, CI 77492, CI 77499)

OTHER INFORMATION

Protect this product from excessive heat and direct sun

QUESTIONS OR COMMENTS?

Call toll free 1-888-498-9004